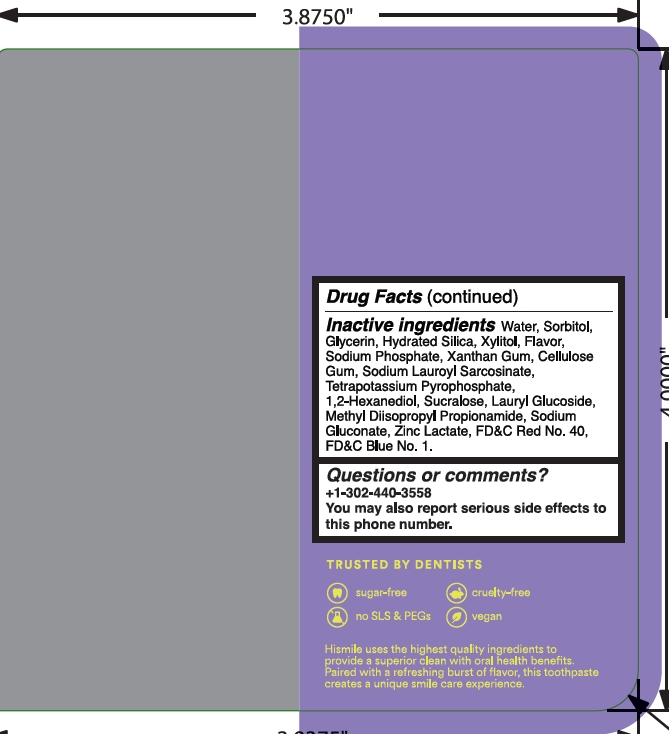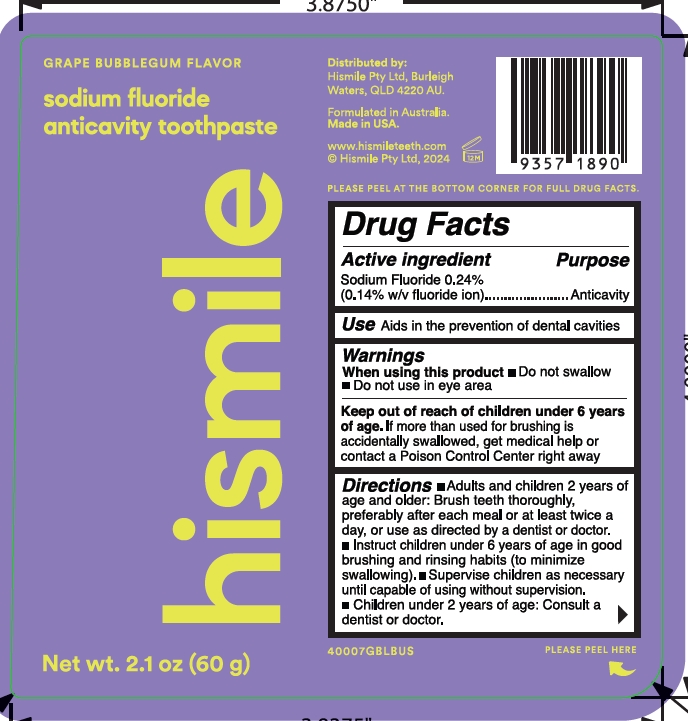 DRUG LABEL: Hismile Grape Bubblegum Flavor Sodium Fluoride Anticavity Toothpast
NDC: 83013-331 | Form: GEL
Manufacturer: Hismile Pty Ltd
Category: otc | Type: HUMAN OTC DRUG LABEL
Date: 20250313

ACTIVE INGREDIENTS: SODIUM FLUORIDE 0.243 g/100 g
INACTIVE INGREDIENTS: SORBITOL; 1,2-HEXANEDIOL; LAURYL GLUCOSIDE; SODIUM GLUCONATE; FD&C RED NO. 40; XYLITOL; SODIUM PHOSPHATE; CELLULOSE GUM; TETRAPOTASSIUM PYROPHOSPHATE; METHYL DIISOPROPYL PROPIONAMIDE; HYDRATED SILICA; GLYCERIN; XANTHAN GUM; SUCRALOSE; ZINC LACTATE; FD&C BLUE NO. 1; SODIUM LAUROYL SARCOSINATE; WATER

Hismile Grape Bubblegum Flavor Sodium Fluoride Anticavity Toothpaste

Active Ingredient

Sodium fluoride 0.24%

(0.14% w/v fluoride ion)

Purpose

Anticavity

Use

Aids in the prevention of dental cavities

Warnings

Keep out of reach of children under 6 years. If more than used for brushing is accidentally swallowed, get medical help or contact a Poison COntrol Center right away.

When using this product

Do not swallow

Do not use in eye area

Directions

- Adults and children 2 years of age and older: Brush teeth thoroughly, preferably after each meal or at least twice a day, or use as directed by a dentist or doctor.
- Instruct children under 6 years of age in good brushing and rinsing habits (to minimize swallowing).
- Supervise children as necessary until capable of using without supervision.
- Children under 2 years of age: Consult a dentist or doctor.

Inactive ingredients

Water

Sorbitol

Glycerin

Hydrated Silica

Xylitol

Sodium Phosphate

Xanthan Gum

Cellulose Gum

Sodium Lauroyl Sarcosinate

Tetrapotassium Pyrophosphate

1,2-Hexanediol

Sucralose

Lauryl Glucoside

Sodium Fluoride

Methyl Diisopropyl Propionamide

Sodium Gluconate

Zinc Lactate

FD&C Red No.40

FD&C Blue No.1